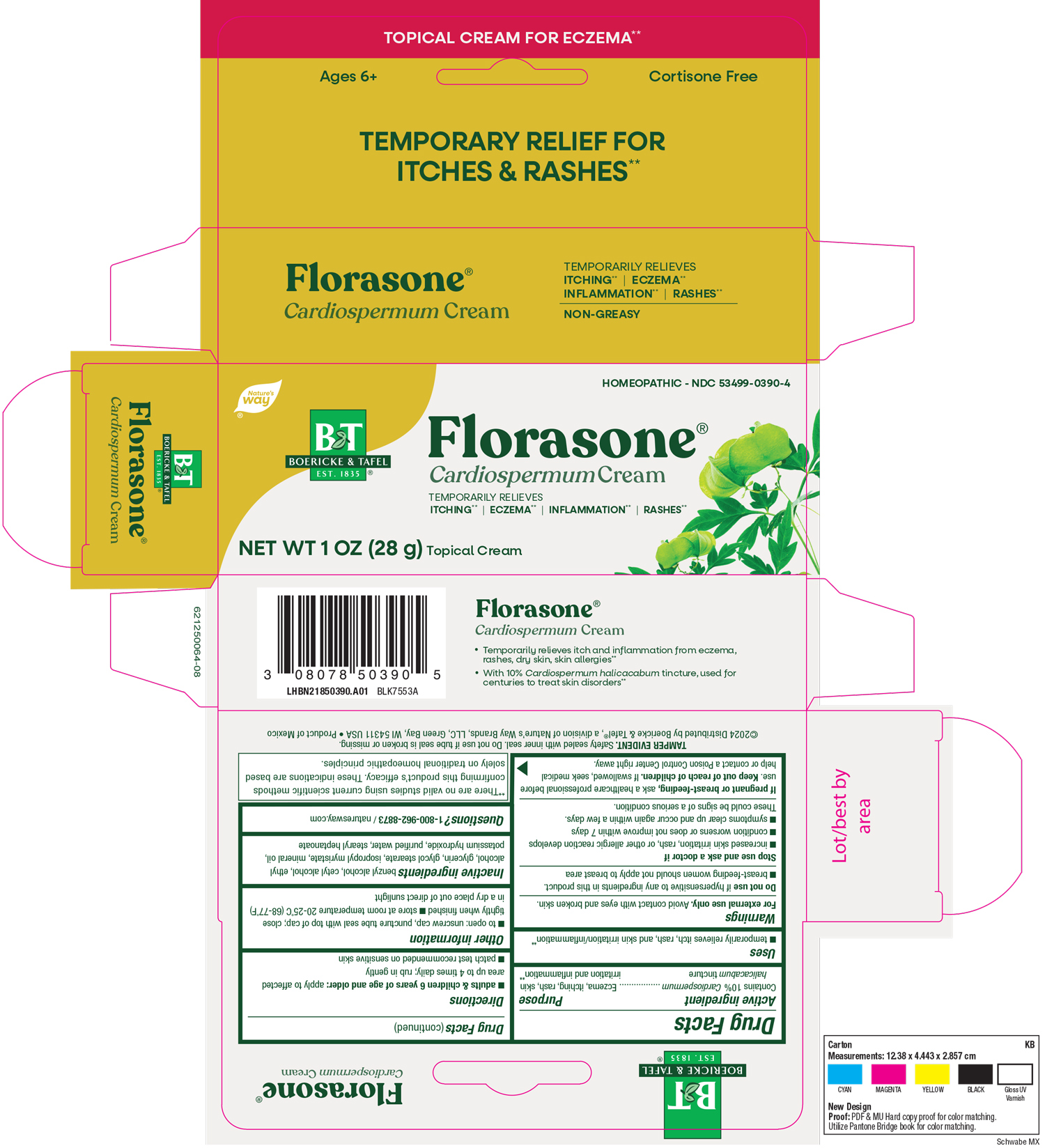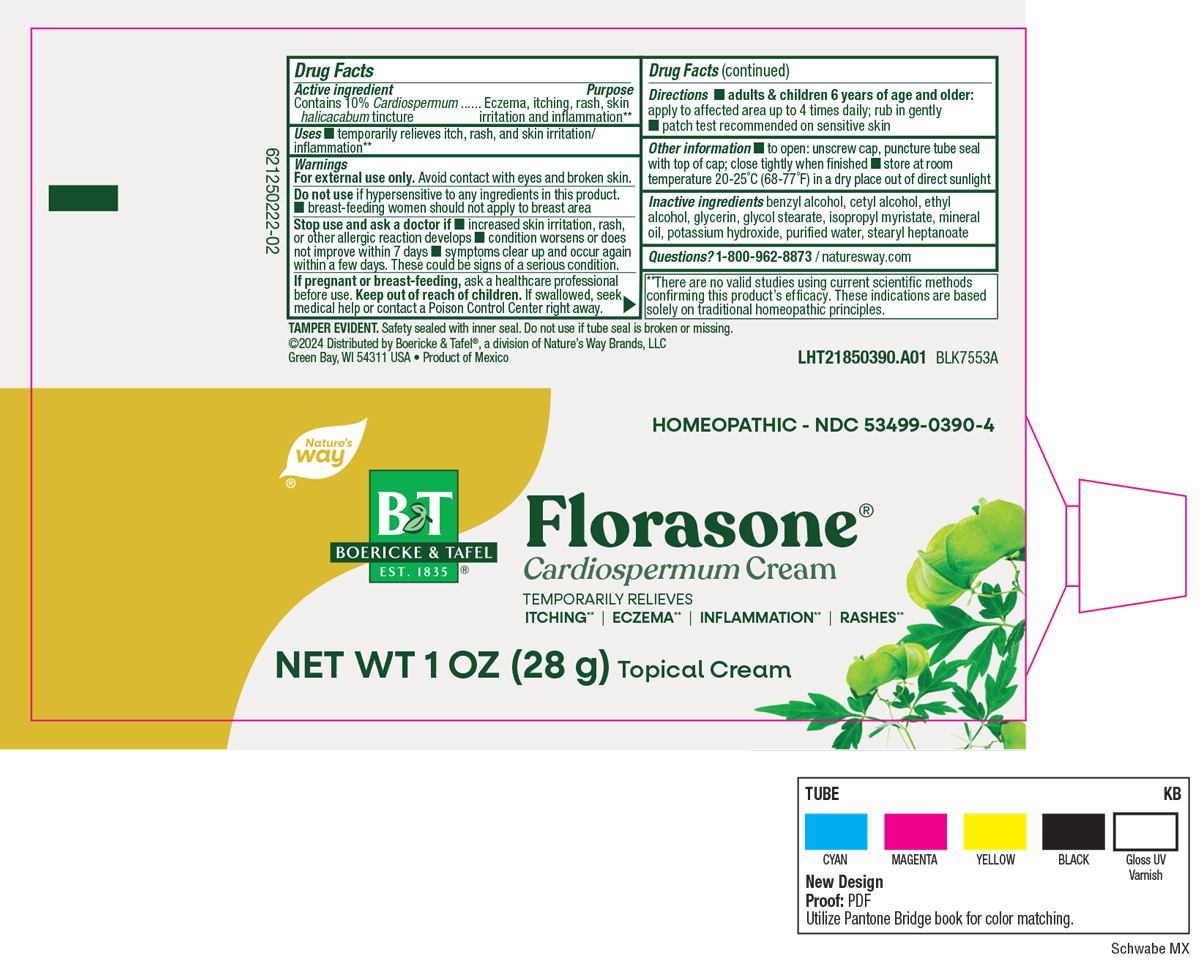 DRUG LABEL: Florasone Cream
NDC: 68466-0003 | Form: CREAM
Manufacturer: Schwabe Mexico, S.A. de C.V.
Category: homeopathic | Type: HUMAN OTC DRUG LABEL
Date: 20251118

ACTIVE INGREDIENTS: CARDIOSPERMUM HALICACABUM FLOWERING TOP 1 [hp_X]/28 g
INACTIVE INGREDIENTS: BENZYL ALCOHOL; CETYL ALCOHOL; GLYCOL STEARATE; GLYCERIN; ISOPROPYL MYRISTATE; MINERAL OIL; POTASSIUM HYDROXIDE; WATER; STEARYL HEPTANOATE; ALCOHOL

Florasone Cream

Active Ingredient

Contains 10% Cardiospermum halicacabum Tincture

Inactive Ingredients

Benzyl Alcohol

Cetyl Alcohol

Ethyl Alcohol

Glycerin

Glycol Stearate

Isopropyl Myristate

Mineral Oil

Potassium Hydroxide

Purified water

Stearyl Heptanoate

Dosage and Administration

Directions

Adults & children 6 years of age and older: apply to affected area up to 4 times daily. Rub in gently.

Patch test recommended on sensitive skin.

Indications and Usage

Temporarily relieves itch, rash, and skin irritation/inflammation.

Purpose

Temporarily relieves itch, rash, and skin irritation/inflammation.

Warnings

For external use only. Avoid contact with eyes and broken skin.

Do not use if hypersensitive to any ingredients in this product.

Breasting-feeding women should not apply to breast area.

Stop Use

Stop use and ask a doctor if increased skin irritation, rash, or other allergic reaction develops, condition worsens or does not improve within 7 days, symptoms clear up and occur again within a few days.

These could be signs of a serious condition.

Pregnancy or Breast Feeding

If pregnant or breast-feeding, ask a healthcare professional before use.

Keep out of reach of Children

Overdosage

If swallowed, seek medical help or contact a Poison Control Center right away.